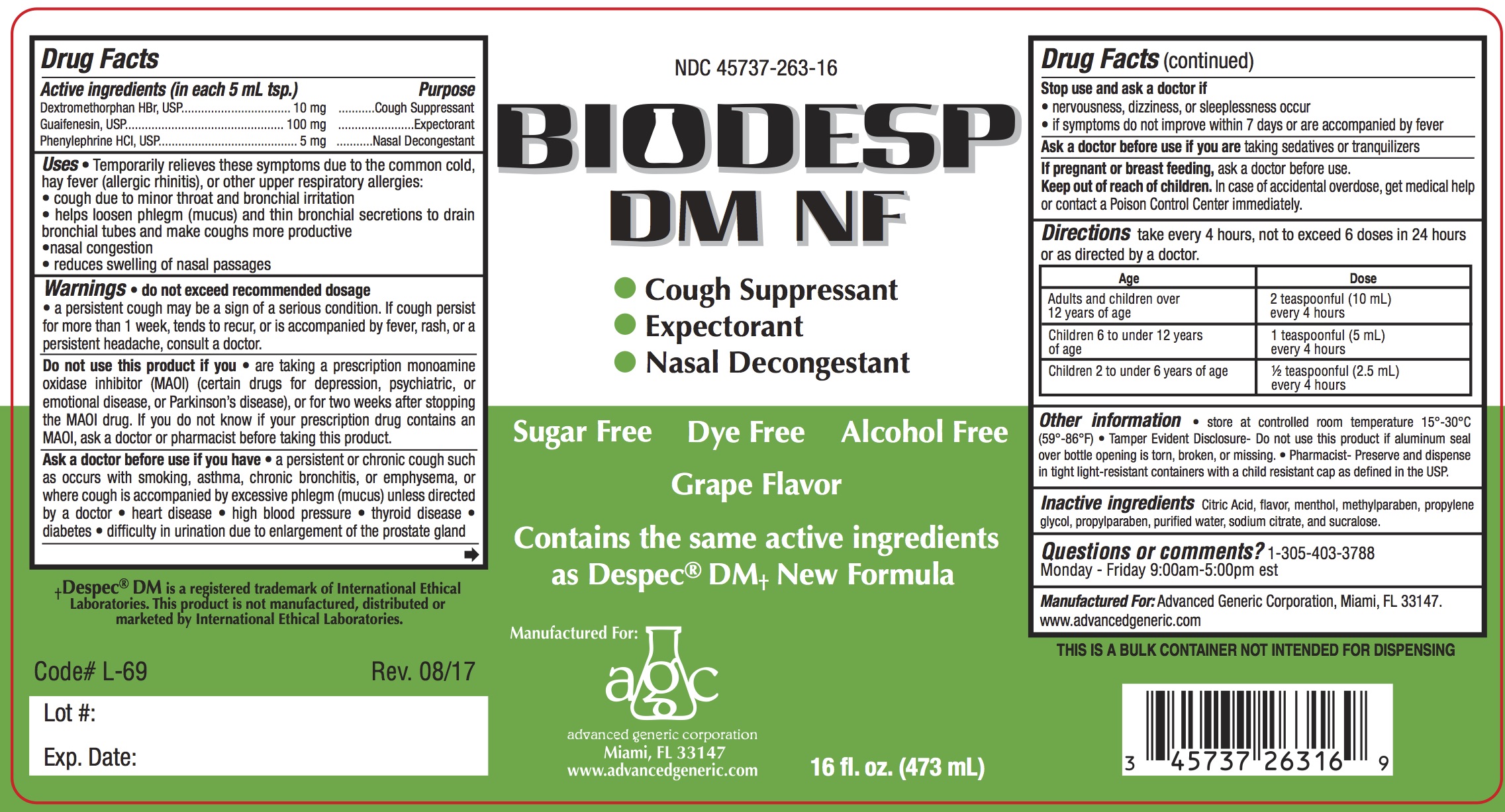 DRUG LABEL: Biodesp
NDC: 45737-263 | Form: LIQUID
Manufacturer: Advanced Generic Corporation
Category: otc | Type: HUMAN OTC DRUG LABEL
Date: 20241220

ACTIVE INGREDIENTS: DEXTROMETHORPHAN HYDROBROMIDE 15 mg/5 mL; GUAIFENESIN 100 mg/5 mL; PHENYLEPHRINE HYDROCHLORIDE 5 mg/5 mL
INACTIVE INGREDIENTS: ANHYDROUS CITRIC ACID; MENTHOL; METHYLPARABEN; PROPYLPARABEN; PROPYLENE GLYCOL; WATER; SUCRALOSE; SODIUM CITRATE

AGC-BiodespDMNF 263

Active Ingredients (in each 5mL) Purpose

Dextromethorphan HBr, 10 mg ................................. Cough Suppressant

Guaifenesin, 100 mg ................................................ Expectorant

Phenylephrine HCl, 5 mg ...................................... Nasal Decongestant

Purpose

Cough Suppressant

Expectorant

Nasal Decongestant

Uses

- temporarily relieves these symptoms due to the common cold, hay fever (allergic rhinitis), or other upper respiratory allergies:
- cough due to minor throat and bronchial irritation
- helps loosen phlegm (mucus) and thin bronchial secretions to drain bronchial tubes and make coughs more productive
- nasal congestion
- reduces swelling of nasal passages

Warnings:

Do no exceed recommended dosage

- A persistent cough may be a sign of a serious condition. If cough persists for more than 1 week, tends to recur or is accompanied by a fever, rash or a persistent headache, consult a doctor

Do not use this product if you

are now taking a prescription monoamine oxidase inhibitor (MAOI) (certain drugs for depression, psychiatric or emotional condition. or for two weeks after stopping the MAOI drug. If you do not know if your prescription drug contains a MAOI, ask a doctor or phamacist before taking thie product.

Ask a doctor before use if you have

- a persistent or chronic cough such as occurs with smoking, asthma, chronic bronchitis, or emphysema, or where cough is accompanied by excessive phlegm (mucus) unless directed by a doctor.
- high blood pressure
- heart disease
- thyroid disease
- diabetes
- difficulty in urincation due to enlargment of the prostate gland unless directed by a doctor

Stop use and ask a doctor if

- nervousness, dizziness, or sleeplessness occur

- if symptoms do not improve within 7 days or are accompanied by fever

Ask a doctor before use if you aretaking sedatives or tranquilizers

KEEP OUT OF REACH OF CHILDREN

Keep out of the reach of children.In case of accidental overdose, get medical help or contact a Poison Control Center immediately.

PREGNANCY OR BREAST FEEDING

If pregnant or breast-feeding, ask a doctor before use

DOSAGE AND ADMINISTRATION

Directions: take every 4 hours, not to exceed 6 doses in 24 hours or as directed by a doctor.

Age | Dose
Adults and children 12 years of age and over | 2 teaspoonfuls (10 mL) every 4 hours
Children 6 to under 12 years of age | 1 teaspoonful (5 mL) every 4 hours
Children under 6 years of age | 1/2 teaspoonful (2.5 mL) every 4 hours to consult a doctor

INACTIVE INGREDIENT

Inactive ingredients: citric acid, flavor, menthol, methylparaben, propylene glycol, propylparaben, pruified water, sodium citrate, and sucralose.

Questions or comments?1-305-403-3788